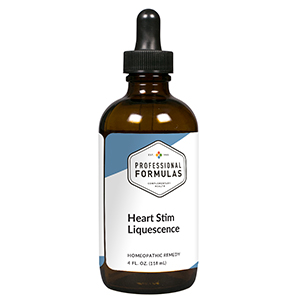 DRUG LABEL: Heart Stim Liquescence
NDC: 63083-3010 | Form: LIQUID
Manufacturer: Professional Complementary Health Formulas
Category: homeopathic | Type: HUMAN OTC DRUG LABEL
Date: 20190815

ACTIVE INGREDIENTS: HAWTHORN LEAF WITH FLOWER 2 [hp_X]/118 mL; TAURINE 2 [hp_X]/118 mL; SELENICEREUS GRANDIFLORUS STEM 3 [hp_X]/118 mL; GINKGO 3 [hp_X]/118 mL; MAGNESIUM PHOSPHATE, DIBASIC TRIHYDRATE 4 [hp_X]/118 mL; SODIUM TETRACHLOROAURATE 6 [hp_X]/118 mL; BEEF HEART 6 [hp_X]/118 mL; VALERIAN 6 [hp_X]/118 mL; UBIDECARENONE 12 [hp_X]/118 mL; DIGITALIS 12 [hp_X]/118 mL
INACTIVE INGREDIENTS: ALCOHOL; WATER

T10

ACTIVE INGREDIENTS

Crataegus oxyacantha 2X
Taurine 2X
Cactus grandiflorus 3X
Ginkgo biloba 3X
Magnesia phosphorica 4X
Aurum muriaticum natronatum 6X
Heart 6X
Valeriana officinalis 6X
Coenzyme Q10 12X
Digitalis purpurea 12X

QUESTIONS

Professional Formulas

PO Box 2034 Lake Oswego, OR 97035

INDICATIONS

For the temporary relief of mild abdominal or chest pain, muscle cramps or spasms, exhaustion, general weakness, dizziness, or anxiousness.*

PURPOSE

*Claims based on traditional homeopathic practice, not accepted medical evidence. Not FDA evaluated.

WARNINGS

Seek medical attention immediately for severe symptoms such as chest pressure or tightness with radiation of the pain to the jaw and down the arm, shortness of breath, or sweating. Keep out of the reach of children. In case of overdose, get medical help or contact a poison control center right away. If pregnant or breastfeeding, ask a healthcare professional before use.

Keep out of the reach of children.

PREGNANCY OR BREAST FEEDING

If pregnant or breastfeeding, ask a healthcare professional before use.

DIRECTIONS

Place drops under tongue 30 minutes before/after meals. Adults and children 12 years and over: Take one full dropper up to 2 times per day. Consult a physician for use in children under 12 years of age.

OTHER INFORMATION

Tamper resistant. If seal is broken, do not use. After opening, close container tightly and store at room temperature away from heat.

INACTIVE INGREDIENTS

20% ethanol, purified water.

LABEL

Est 1985

Professional Formulas

Complementary Health

Heart Stim Liquescence

Homeopathic Remedy

4 FL. OZ. (118 mL)